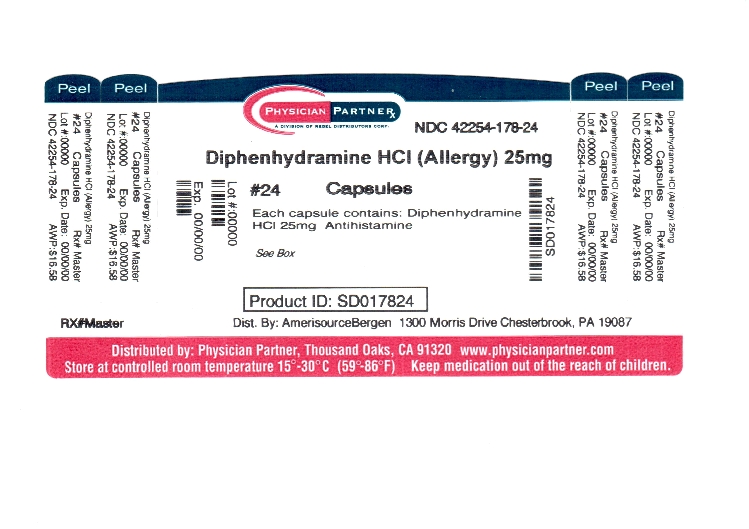 DRUG LABEL: good neighbor pharmacy allergy
NDC: 42254-178 | Form: CAPSULE
Manufacturer: Rebel Distributors Corp
Category: otc | Type: HUMAN OTC DRUG LABEL
Date: 20120313

ACTIVE INGREDIENTS: DIPHENHYDRAMINE HYDROCHLORIDE 25 mg/1 1
INACTIVE INGREDIENTS: BENZYL ALCOHOL; BUTYLPARABEN; D&C RED NO. 28; D&C YELLOW NO. 10; EDETATE CALCIUM DISODIUM; FD&C BLUE NO. 1; FD&C BLUE NO. 2; FD&C RED NO. 40; GELATIN; LACTOSE; MAGNESIUM STEARATE; METHYLPARABEN; POLYSORBATE 80; PROPYLPARABEN; SILICON DIOXIDE; SODIUM LAURYL SULFATE; SODIUM PROPIONATE

Amerisource Bergen Allergy Capsules Drug Facts

Active ingredient (in each capsule)

Diphenhydramine hydrochloride 25 mg

Purpose

Antihistamine

Uses

- temporarily relieves these symptoms due to hay fever or other upper respiratory allergies:
- runny nose
- sneezing
- itchy, watery eyes
- itchy nose or throat
- temporarily relieves these symptoms of the common cold:
- runny nose
- sneezing

Warnings

Do not use

- with any other product containing diphenhydramine, even one used on skin
- to make a child sleepy

Ask a doctor before use if you have

- trouble urinating due to an enlarged prostate gland
- glaucoma
- a breathing problem such as emphysema or chronic bronchitis

Ask a doctor or pharmacist before use if you are

taking tranquilizers or sedatives

When using this product

- excitability may occur, especially in children
- marked drowsiness may occur
- avoid alcoholic drinks
- alcohol, sedatives and tranquilizers may increase drowsiness
- be careful when driving a motor vehicle or operating machinery

If pregnant or breast-feeding,

ask a health professional before use.

Keep out of reach of children.

In case of overdose, get medical help or contact a Poison Control Center right away.

Directions

- take every 4 to 6 hours, not more than 6 doses in 24 hours

adults and children 12 years of age and over | 1 or 2 capsules
children 6 to under 12 years of age | 1 capsule
children 4 to under 6 years of age | do not use unless directed by a doctor
children under 4 years of age | do not use

Other information

- store at room temperature (59°-86°F)
- protect from moisture

Inactive ingredients

benzyl alcohol, butylparaben, D&C red no. 28, D&C yellow no. 10, edetate calcium disodium, edible ink, FD&C blue no. 1, FD&C blue no. 2, FD&C red no. 40, gelatin, lactose, magnesium stearate, methylparaben, polysorbate 80, propylparaben, silicon dioxide, sodium lauryl sulfate, sodium propionate

Questions or comments?

1-800-719-9260

Principal Display Panel

Compare to active ingredient in Benadryl® Allergy Kapseals®

See New Warning and Dosing Directions

Allergy

Diphenhydramine HCl

Antihistamine

Easy to Swallow

For Allergy Relief

Sneezing

Itchy, Watery Eyes

Runny Nose

Itchy Throat